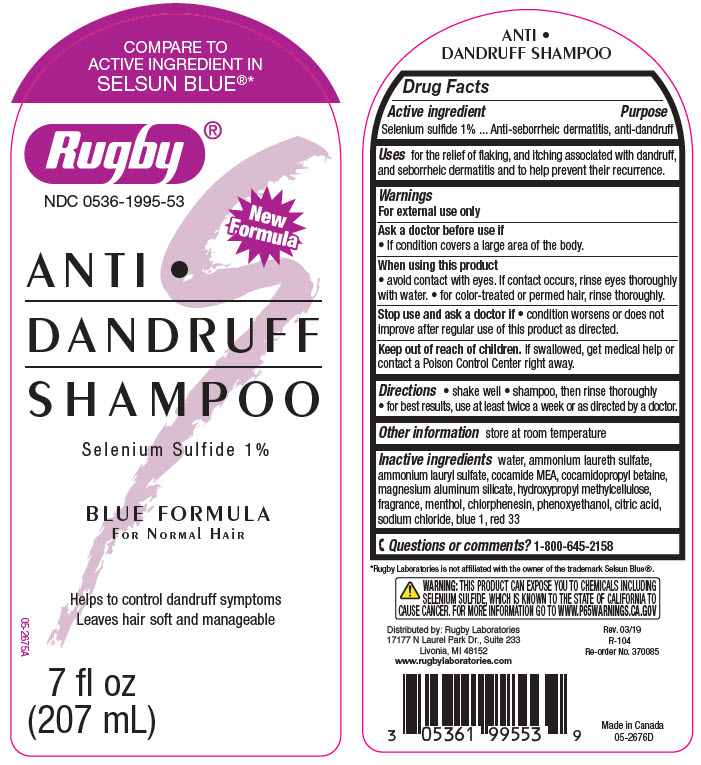 DRUG LABEL: Rugby Anti-Dandruff
NDC: 0536-1995 | Form: SHAMPOO
Manufacturer: Rugby Laboratories
Category: otc | Type: HUMAN OTC DRUG LABEL
Date: 20240314

ACTIVE INGREDIENTS: Selenium Sulfide 10 mg/1 mL
INACTIVE INGREDIENTS: Water; Ammonium Laureth-2 Sulfate; Ammonium Lauryl Sulfate; COCO MONOETHANOLAMIDE; Cocamidopropyl Betaine; Coco Diethanolamide; Magnesium Aluminum Silicate; HYPROMELLOSE, UNSPECIFIED; Menthol, unspecified form; Chlorphenesin; Phenoxyethanol; DMDM Hydantoin; Citric Acid Monohydrate; Sodium Chloride; Fd&C Blue No. 1; D&C Red No. 33

Rugby® Anti-Dandruff

Drug Facts

Active ingredient

Selenium Sulfide 1%

Purpose

Anti-seborrheic dermatitis, anti-dandruff

Uses

for the relief of flaking and itching associated with dandruff and seborrheic dermatitis and to help prevent their recurrence.

Warnings

For external use only

As a doctor before use if

- condition covers a large area of the body.

When using this product

- avoid contact with the eyes. If contact occurs, rinse eyes thoroughly with water.
- for color-treated or permed hair, rinse thoroughly.

Stop use and ask a doctor if

- condition worsens or does not improve after regular use of this product as directed.

Keep out of reach of children. If swallowed, get medical help or contact a Poison Control Center right away.

Directions

- shake well
- shampoo, then rinse thoroughly
- for best results, use at least twice a week or as directed by a doctor.

Other information

store at room temperature

Inactive ingredients

water, ammonium laureth sulfate, ammonium lauryl sulfate, cocamide MEA, cocamidopropyl betaine, magnesium aluminum silicate, hydroxypropyl methylcellulose, fragrance, menthol, chlorphenesin, phenoxyethanol, citric acid, sodium chloride, blue 1, red 33

Questions or comments?

1-866-645-2158

Distributed by: Rugby Laboratories
17177 N Laurel Park Dr., Suite 233
Livonia, MI 48152

PRINCIPAL DISPLAY PANEL - 207 mL Bottle Label

COMPARE TO
ACTIVE INGREDIENT IN
SELSUN BLUE®*

Rugby®

NDC 0536-1995-53

New
Formula

ANTI •
DANDRUFF
SHAMPOO

Selenium Sulfide 1%

BLUE FORMULA
FOR NORMAL HAIR

Helps to control dandruff symptoms
Leaves hair soft and manageable

7 fl oz
(207 mL)

05-2675A